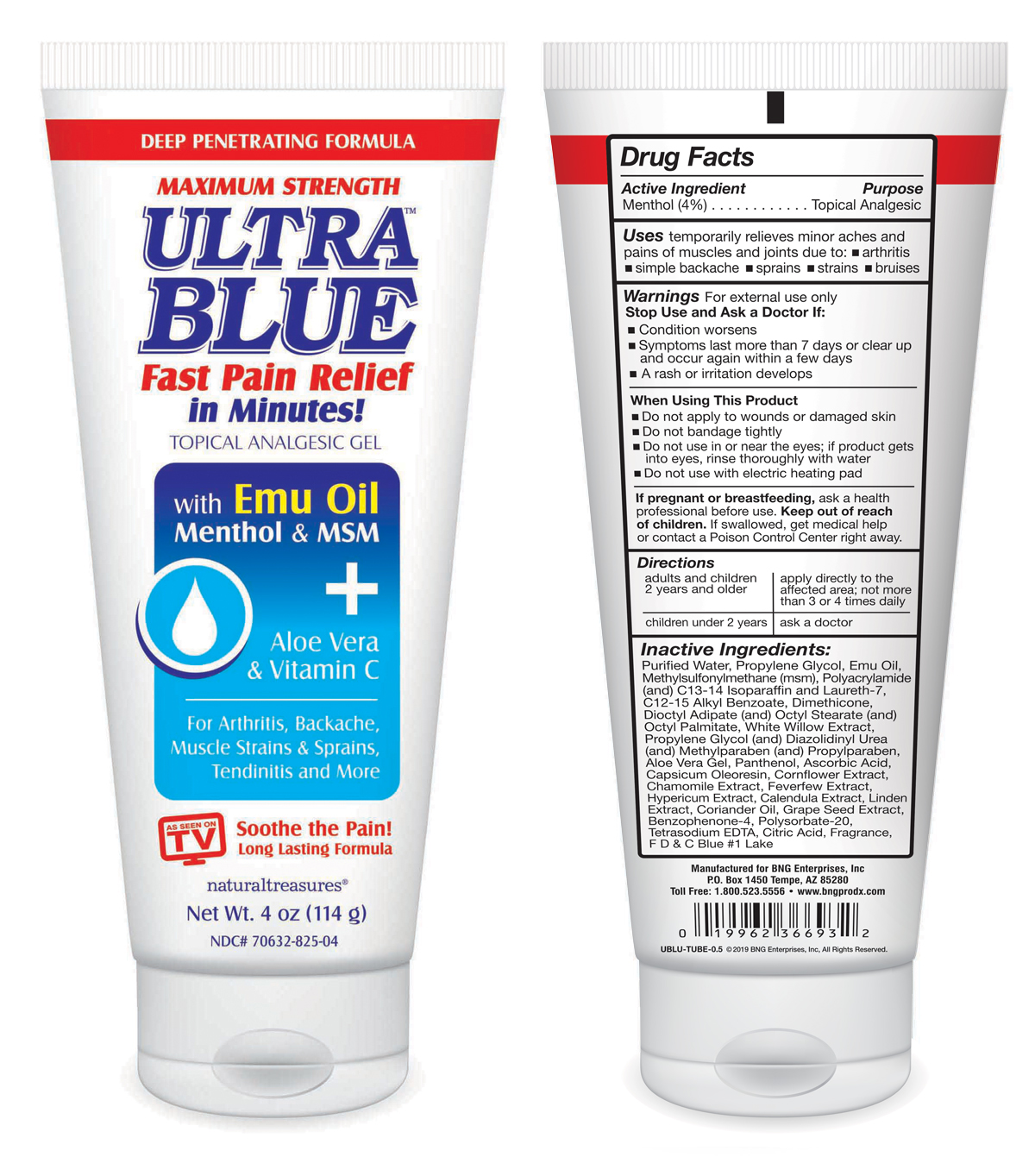 DRUG LABEL: Ultra Blue
NDC: 70632-825 | Form: GEL
Manufacturer: BNG Enterprises DBA Herbal Clean
Category: otc | Type: HUMAN OTC DRUG LABEL
Date: 20190419

ACTIVE INGREDIENTS: MENTHOL, UNSPECIFIED FORM 4.56 g/114 g
INACTIVE INGREDIENTS: EMU OIL

Active ingredient section

Menthol (4%)

Purpose

Topical Analgesic

Uses:

Temporarily relieves minor aches and pains of muscles and joints due to arthritis, simple backache, sprains, strains, bruises.

Warnings

For external use only.

Stop Use and Ask a Doctor If

• Condition worsens

• Symptoms last more than 7 days or clear up and occur again within a few days

• A rash or irritation develops

Keep out of reach of children

If pregnant or breastfeeding, ask a health professional before use. Keep out of reach of children. If swallowed, get medical help or contact a Poison Control Center right away.

When Using This Product

• Do not apply to wounds or damaged skin

• Do not bandage tightly

• Do not use in or near the eyes; if product gets into eyes, rinse thoroughly with water

• Do not use with electric heating pad

Directions

• Adults and children 2 years and older, apply directly to affected area; not more than 3 or 4 times daily

• Children under 2 years, ask a doctor

Inactive Ingredients:

Purified Water, Propylene Glycol, Emu Oil, Methylsulfonylmethane (msm), Polyacrylamide (and) C13-14 Isoparaffin and Laureth-7, C12-15 Alkyl Benzoate, Dimethicone, Dioctyl Adipate (and) Octyl Stearate (and) Octyl Palmitate, White Willow Extract, Propylene Glycol (and) Diazolidinyl Urea (and) Methylparaben (and) Propylparaben, Aloe Vera Gel, Panthenol, Ascorbic Acid, Capsicum Oleoresin, Cornflower Extract, Chamomile Extract, Feverfew Extract, Hypericum Extract, Calendula Extract, Linden Extract, Coriander Oil, Grape Seed Extract, Benzophenone-4, Polysorbate-20, Tetrasodium EDTA, Citric Acid, Fragrance, F D & C Blue #1 Lake